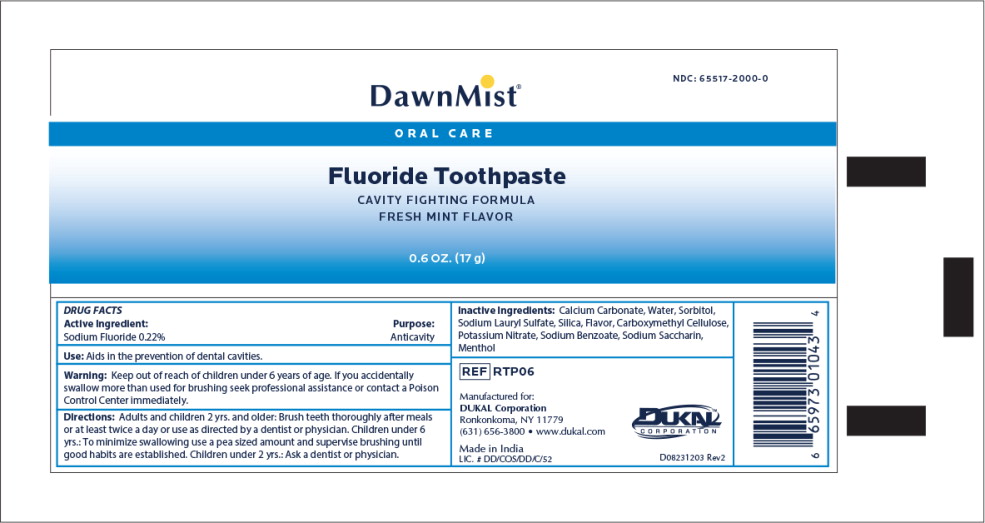 DRUG LABEL: Sodium fluoride
NDC: 65517-2000 | Form: CREAM
Manufacturer: DUKAL LLC
Category: otc | Type: HUMAN OTC DRUG LABEL
Date: 20240708

ACTIVE INGREDIENTS: SODIUM FLUORIDE 0.22 g/100 g
INACTIVE INGREDIENTS: CALCIUM CARBONATE; WATER; SORBITOL; SODIUM LAURYL SULFATE; SILICON DIOXIDE; CARBOXYMETHYLCELLULOSE; POTASSIUM NITRATE; SODIUM BENZOATE; SACCHARIN SODIUM; MENTHOL

DAWNMIST TOOTHPASTE

Active ingredient

Sodium fluoride 0.22%

Purpose

Anticavity

Use

aids in the prevention of dental cavities

Warnings Section

Warnings

Keep out of reach of children under six years of age. If you accidently swallow more than used for brushing seek professional assistance or contact a Poison Control Center immediately

Directions

Adults and children 2 years: and older: Brush teeth thoroughly after meals or at least twice a day or use as directed by a dentist or physician.

Children under 6 years: To minimize swallowing use a pea sized amount and supervise brushing until good habits are established.

Children under 2 years: Ask a doctor or physician.

Inactive ingredients

calcium carbonate,water,sorbitol, sodium lauryl sulfate, silica, carboxymethyl cellulose, flavor, potassium nitrate, sodium benzoate, sodium saccharin, menthol

Expiration date

Expiration date & batch No. on crimp of tube

Principal Display Panel - DawnMist Fluoride Toothpaste 0.6 OZ Tube Label

DawnMist®

NDC: 65517-2000-0

ORAL CARE

Fluoride Toothpaste

CAVITY FIGHTING FORMULA

FRESH MINT FLAVOR

0.6 OZ. (17 g)